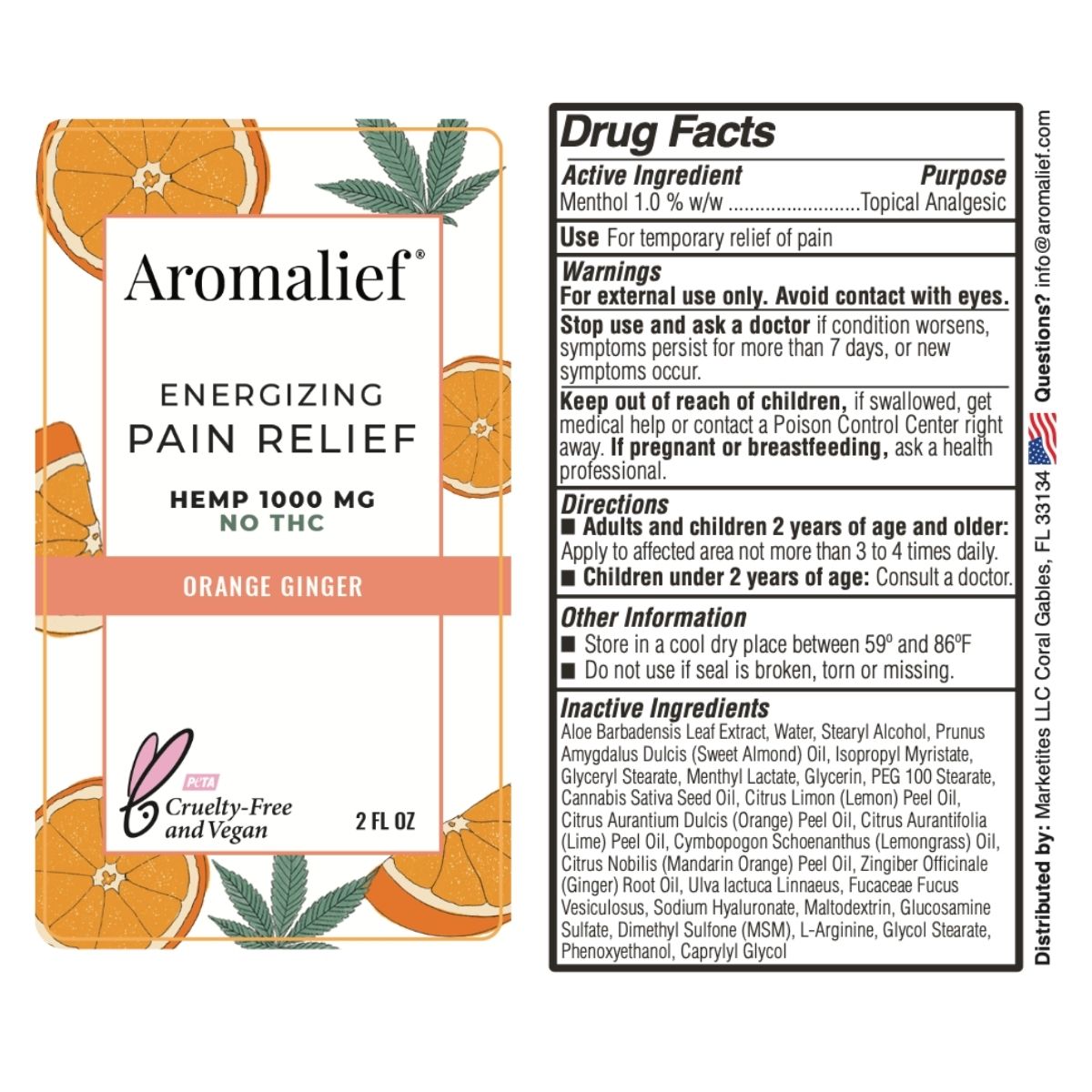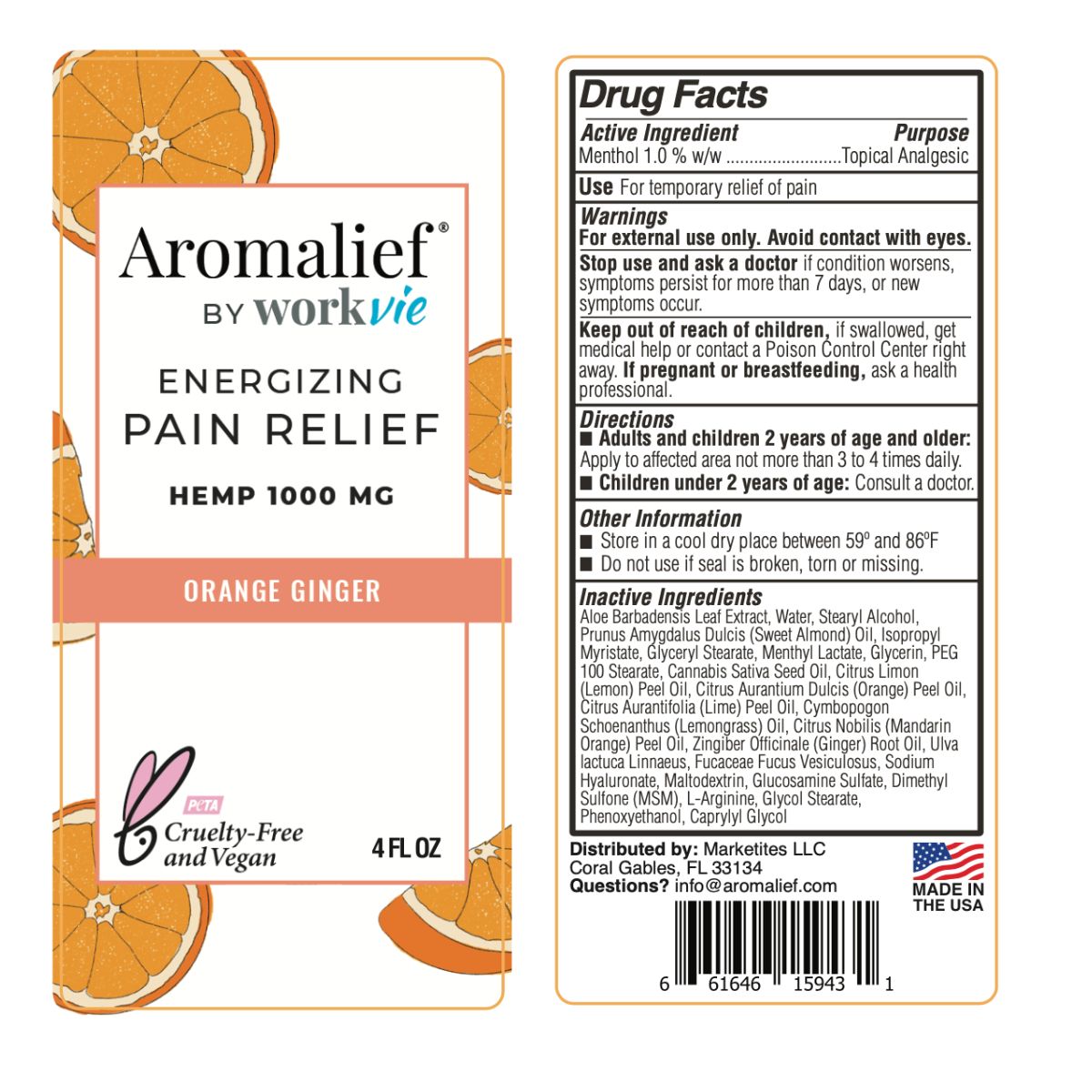 DRUG LABEL: Aromalief Pain Relief Cream Orange Ginger
NDC: 72393-301 | Form: LOTION
Manufacturer: Marketites LLC
Category: otc | Type: HUMAN OTC DRUG LABEL
Date: 20251029

ACTIVE INGREDIENTS: MENTHOL 1 g/100 g
INACTIVE INGREDIENTS: CITRUS AURANTIIFOLIA FRUIT OIL; CITRUS AURANTIUM FRUIT RIND; ZINGIBER OFFICINALE WHOLE; DIMETHYL SULFONE; CYMBOPOGON SCHOENANTHUS OIL; CANNABIS SATIVA SEED OIL; GLYCERIN; MALTODEXTRIN; GLUCOSAMINE SULFATE; ARGININE; CAPRYLYL GLYCOL; CITRUS LIMON FRUIT OIL; PEG-100 STEARATE; HYALURONATE SODIUM; ULVA LACTUCA; GLYCOL STEARATE; FUCUS VESICULOSUS; ALOE VERA LEAF; GLYCERYL STEARATE SE; PHENOXYETHANOL; STEARYL ALCOHOL; ISOPROPYL MYRISTATE; ALMOND OIL; MENTHYL LACTATE, (-)-; CITRUS NOBILIS

Aromalief Orange

Active Ingredients

Menthol 1.0% w/w

Purpose

Topical Analgesic

Uses

For temporary relief of pain.

Warnings

For external use only. Avoid contact with eyes.

Stop use and ask a doctor if condition worsens, or if symptoms persist for more than 7 days, or new symptoms occur.

Keep out of reach of children, if swallowed, get medical help or contact a Poison Control Center right away.

If pregnant or breastfeeding, ask a health professional.

Directions

Adults and children 2 years of age and older: Apply to affected area not more than 3 to 4 times daily. Children under 2 years of age: consult a doctor.

Other Information

Store in a cool dry place between 68º and 77ºF and relative humidity not exceeding 65%.

Do not use if seal is broken, torn or missing.

Inactive Ingredients

Aloe Barbadensis Leaf Extract, Water, Stearyl Alcohol, Prunus Amygdalus Dulcis (Sweet Almond) Oil, Isopropyl Myristate, Glyceryl Stearate, Menthyl Lactate, Glycerin, PEG 100 Stearate, Cannabis Sativa Seed Oil, Ulva lactuca Linnaeus, Fucaceae Fucus Vesiculosus, Sodium Hyaluronate, Helianthus Annuus (Sunflower) Seed Oil, Lavandula Angustifolia (Lavender) Flower Oil, Lavandula Hybrida (Lavandin) Oil, Citrus Aurantium Bergamia (Bergamot) Fruit Oil, Eucalyptus Globulus Leaf (Eucalyptus) Oil, Pelargonium Graveolens (Geranium) Flower Oil, Maltodextrin, Glucosamine Sulfate, Dimethyl Sulfone (MSM), L-Arginine, Glycol Stearate, Phenoxyethanol, Caprylyl Glycol

Questions or comments

info@aromalief.com